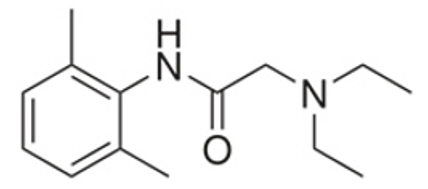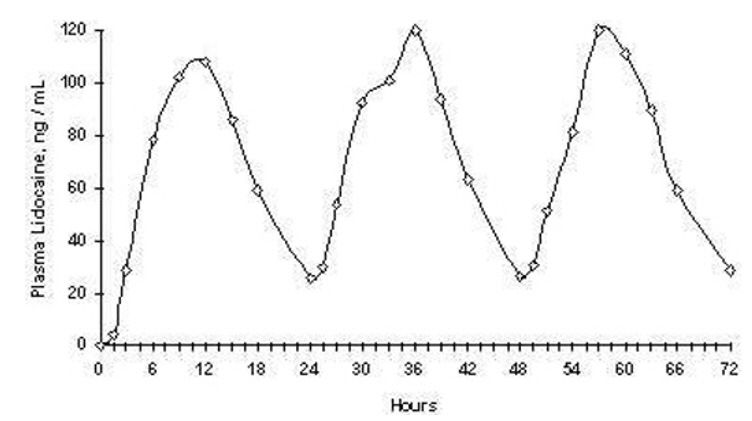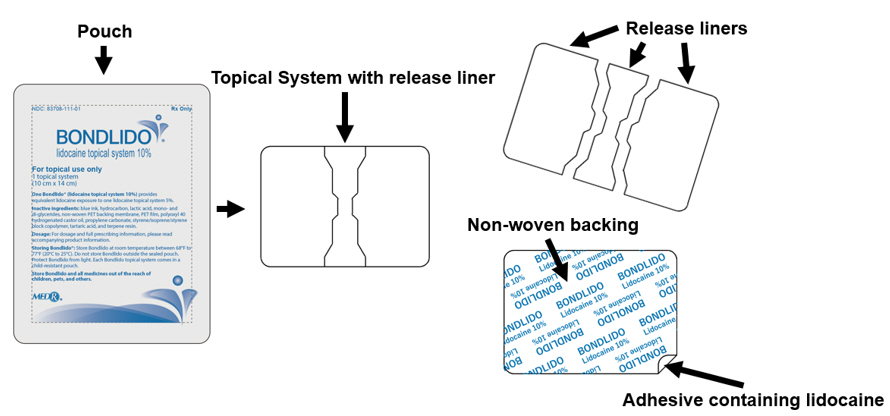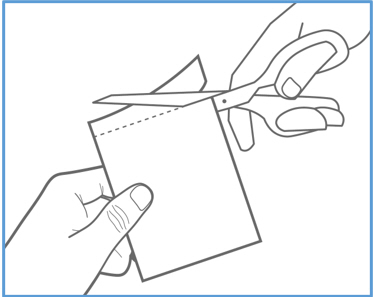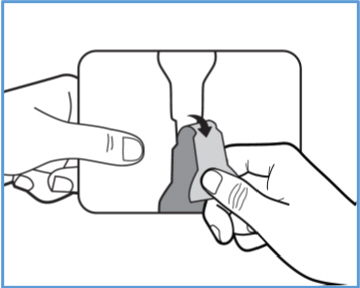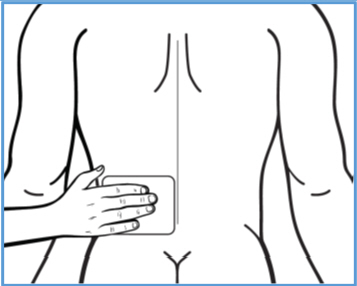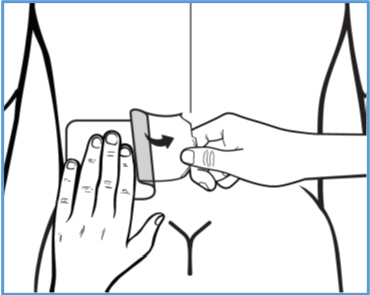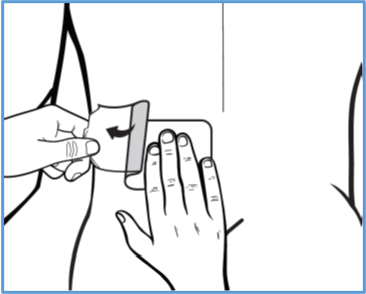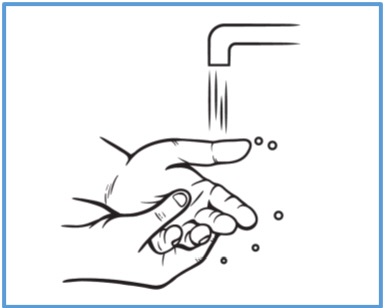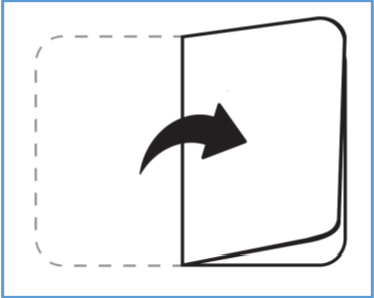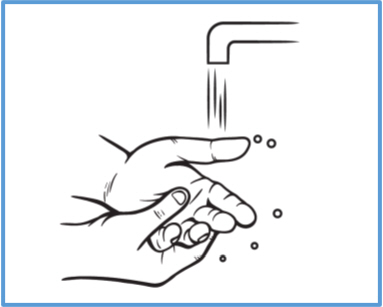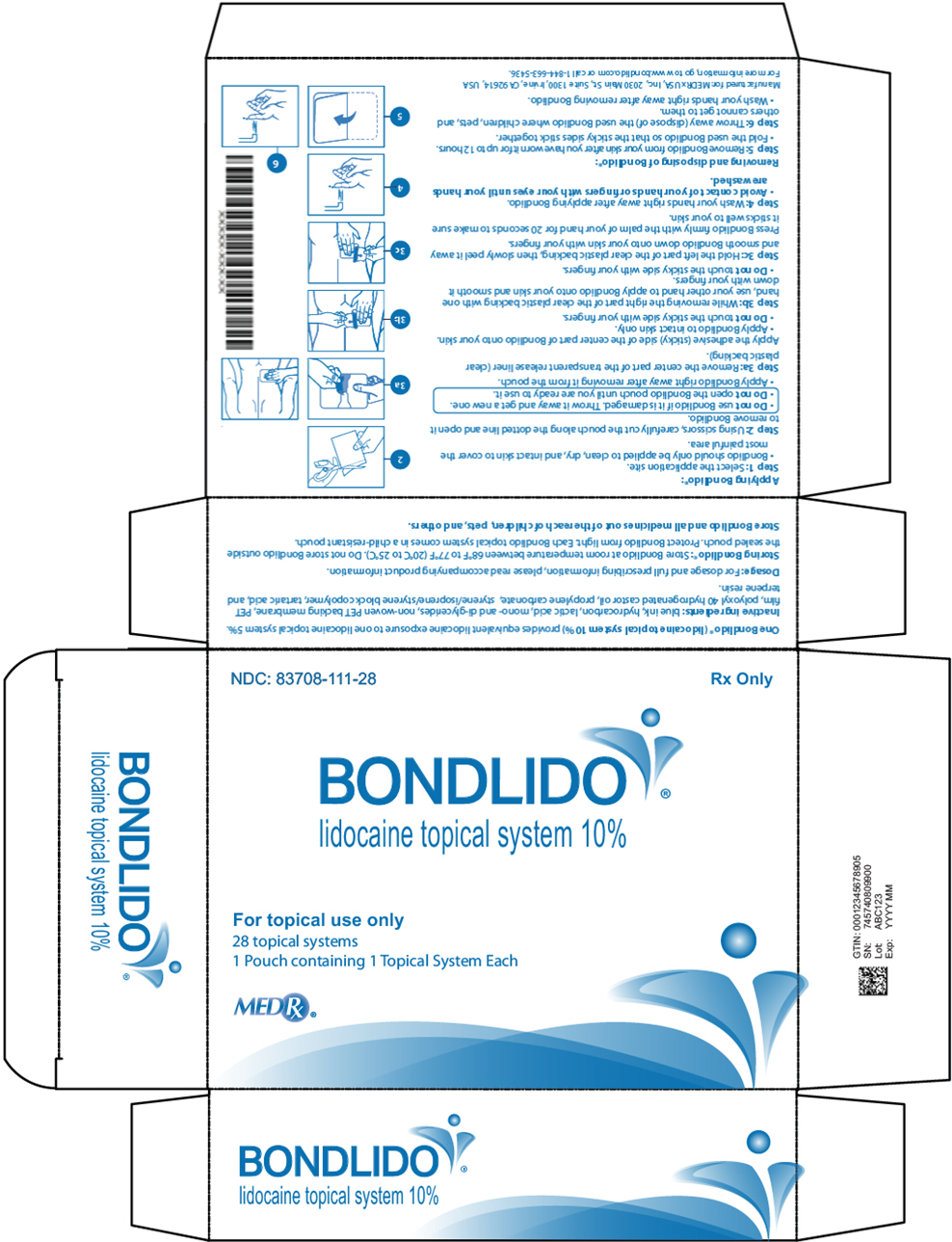 DRUG LABEL: BONDLIDO
NDC: 83708-111 | Form: SYSTEM
Manufacturer: MEDRx USA, Inc.
Category: prescription | Type: HUMAN PRESCRIPTION DRUG LABEL
Date: 20251006

ACTIVE INGREDIENTS: lidocaine 200 mg/1 1
INACTIVE INGREDIENTS: Lactic Acid, Unspecified Form; Glyceryl Mono- and Dipalmitostearate Type B; Polyoxyl 40 hydrogenated castor oil; Propylene carbonate; Styrene/isoprene/styrene block copolymer; Tartaric acid; Terpene resin

HIGHLIGHTS OF PRESCRIBING INFORMATION

These highlights do not include all the information needed to use BONDLIDO® safely and effectively. See full prescribing information for BONDLIDO®.
BONDLIDO (lidocaine topical system)
Initial U.S. Approval: 1953

1 INDICATIONS AND USAGE

BONDLIDO contains lidocaine, an amide local anesthetic, and is indicated in adults for relief of pain associated with post-herpetic neuralgia (PHN) (1).

2 DOSAGE AND ADMINISTRATION

- Due to differences in bioavailability, the efficacy of a lidocaine topical system does not necessarily correlate with dosage strength. Refer to the dosing instructions for the specific product being used (2).
- Apply BONDLIDO to intact skin to cover the most painful area. Apply the prescribed number of topical systems (maximum of two) only once for up to 12 hours in a 24-hour period (2).
- Apply firm pressure for 20 seconds to ensure adequate adherence.

3 DOSAGE FORMS AND STRENGTHS

Topical System: 10% lidocaine (3).

4 CONTRAINDICATIONS

BONDLIDO is contraindicated in patients with a known history of sensitivity to local anesthetics of the amide type, or to any other component of the product (4).

5 WARNINGS AND PRECAUTIONS

- Accidental Exposure: A used BONDLIDO topical system contains residual lidocaine after use. It is important for patients to store and dispose of BONDLIDO out of the reach of children, pets, and others (5.1).
- Excessive Dosing: Applying BONDLIDO to larger surface areas or for a longer duration than recommended could result in increased absorption and high blood concentrations of lidocaine, leading to serious adverse effects (5.2).
- Non-Intact Skin: May result in higher blood concentrations of lidocaine from increased absorption (5.2).
- External Heat Sources: External heat sources may increase drug exposure, leading to overexposure of lidocaine (5.2).
- Methemoglobinemia: Cases of methemoglobinemia have been reported in association with local anesthetic use (5.3).
- Application Site Reactions: Severe skin irritation may occur with BONDLIDO if applied for a longer period than instructed (5.4).
- Hypersensitivity Reactions: Patients with an allergy to PABA derivatives may have cross-sensitivity to BONDLIDO(5.5).
- Eye Exposure: If eye contact occurs, immediately wash out the eye with water or saline and protect the eye using, for example, eyeglasses/eye wear, until sensation returns (5.6).

6 ADVERSE REACTIONS

Common adverse reactions are application site reactions such as irritation, erythema, and pruritus (6).

To report SUSPECTED ADVERSE REACTIONS, contact MEDRx USA, Inc. at TELEPHONE or FDA at 1-800-FDA-1088 or www.fda.gov/medwatch.

7 DRUG INTERACTIONS

- Antiarrhythmic Drugs: When BONDLIDO is used in patients receiving Class I antiarrhythmic drugs (such as tocainide or mexiletine), the toxic effects are additive and potentially synergistic. Consider risk/benefit during concomitant use (7.1).
- Local Anesthetics: When BONDLIDO is used concomitantly with other products containing local anesthetic agents, the effects are additive. The amount absorbed from all formulations must be considered for safe use (7.2).

8 USE IN SPECIFIC POPULATIONS

Lactation: Lidocaine is excreted into human milk. Caution should be exercised when BONDLIDO is administered to a nursing mother, especially when administered with other local anesthetics (8.2).

FULL PRESCRIBING INFORMATION

1 INDICATIONS AND USAGE

BONDLIDO (lidocaine topical system 10%) is indicated in adults for relief of pain associated with post-herpetic neuralgia (PHN).

2 DOSAGE AND ADMINISTRATION

2.1 Important Dosage and Administration Information

Due to differences in bioavailability, the efficacy of a lidocaine topical system does not necessarily correlate with dosage strength (i.e., concentration). Comparing different products on a nominal percentage-for-percentage basis may be misleading and the appropriate strength for a given indication may vary by product. Refer to the dosing instructions for the specific product being used. [see Clinical Pharmacology (12.3)].

When BONDLIDO is used concomitantly with other products containing local anesthetic agents, the total amount of drug absorbed from all formulations must be considered.

2.2 Application Instructions

Clearly instruct and advise patients:

- to apply BONDLIDO to intact skin to cover the most painful area. Apply the prescribed number of topical systems (maximum of 2), only once for up to 12 hours within a 24-hour period. Safety has not been established for application of more than 2 BONDLIDO topical systems per day.
- to apply firm pressure for 20 seconds to ensure an adequate adherence.
- that clothing may be worn over the area of application.
- to remove BONDLIDO if irritation or a burning sensation occurs during application. Advise patients not to reapply until the irritation subsides.
- to wash hands immediately after handling BONDLIDO and to avoid contact with eyes [see Warnings and Precautions (5.5), Patient Counseling Information (17)].
- to not store BONDLIDO outside of the sealed pouch.
- to apply immediately after removal from the protective pouch.
- to fold used BONDLIDO so that the adhesive side sticks to itself.
- to safely discard used BONDLIDO where children and pets cannot get to them.
- to never apply external heat sources, such as heating pads or electric blankets, directly to BONDLIDO because plasma lidocaine levels may be increased [see Warnings and Precautions (5.2), Patient Counseling Information (17)].
- that BONDLIDO may not stick if it gets wet and to avoid contact with water, such as bathing, swimming, or showering, while a BONDLIDO topical system is applied. If the BONDLIDO topical system comes off completely and will not stick to the skin, advise patients that they may apply a replacement BONDLIDO topical system and take the replacement BONDLIDO topical system off at the usual removal time. Advise patients not to wear BONDLIDO for more than 12 hours within a 24-hour period.

3 DOSAGE FORMS AND STRENGTHS

BONDLIDO Topical System: 10% lidocaine. BONDLIDO is a rectangular topical system with blue printing on one side and a release liner on other and is packaged in an individual unit-dose pouch.

4 CONTRAINDICATIONS

BONDLIDO is contraindicated in patients with a known history of sensitivity to local anesthetics of the amide type, or to any other component of the product.

5 WARNINGS AND PRECAUTIONS

5.1 Accidental Exposure

A used BONDLIDO topical system contains residual lidocaine after use. The potential exists for a small child or a pet to suffer serious adverse effects from chewing or ingesting new or used BONDLIDO. It is important for patients to store and dispose of BONDLIDO properly, and keep out of the reach of children, pets, and others [see Dosage and Administration (2)].

5.2 Excessive Dosing

Lidocaine toxicity could be expected at lidocaine blood concentrations above 5 µg/mL. The blood concentration of lidocaine is determined by the rate of systemic absorption and elimination. Longer duration of application, application of more than the recommended number of BONDLIDO, smaller patients, or impaired elimination may all contribute to increasing the blood concentration of lidocaine.

If lidocaine overdose is suspected, check drug blood concentration. Management of overdose includes close monitoring, supportive care, and symptomatic treatment [see Overdosage (10)].

Improper Application and Duration of Use: Application of more than the recommended number of BONDLIDO or applying BONDLIDO for longer than the recommended wearing time (12 hours of every 24 hours) could result in increased absorption and high blood concentrations of lidocaine, leading to adverse effects. Advise patients on proper application and duration [see Patient Counseling Information (17)].

Hepatic Disease: Impaired elimination may contribute to increasing blood concentrations of lidocaine. Patients with severe hepatic disease are at greater risk of developing toxic blood concentrations of lidocaine because of their inability to metabolize lidocaine normally.

Non-Intact Skin: Application to broken or inflamed skin, although not tested, may result in higher blood concentrations of lidocaine from increased absorption. BONDLIDO is only recommended for use on intact skin. Advise patients not to apply BONDLIDO to non-intact skin [see Patient Counseling Information (17)].

External Heat Sources: External heat sources may increase drug exposure, leading to overexposure to lidocaine. Advise patients not to apply external heat sources to BONDLIDO during administration [see Patient Counseling Information (17)].

5.3 Methemoglobinemia

Cases of methemoglobinemia have been reported in association with local anesthetic use. Although all patients are at risk for methemoglobinemia, patients with glucose-6-phosphate dehydrogenase deficiency, congenital or idiopathic methemoglobinemia, cardiac or pulmonary compromise, infants under 6 months of age, and concurrent exposure to oxidizing agents or their metabolites are more susceptible to developing clinical manifestations of the condition. If local anesthetics must be used in these patients, close monitoring for symptoms and signs of methemoglobinemia is recommended.

Signs of methemoglobinemia may occur immediately or may be delayed some hours after exposure and are characterized by a cyanotic skin discoloration and/or abnormal coloration of the blood.

Methemoglobin levels may continue to rise; therefore, immediate treatment is required to avert more serious central nervous system and cardiovascular adverse effects, including seizures, coma, arrhythmias, and death. Discontinue BONDLIDO and any other oxidizing agents. Depending on the severity of the signs and symptoms, patients may respond to supportive care, i.e., oxygen therapy, hydration. A more severe clinical presentation may require treatment with methylene blue, exchange transfusion, or hyperbaric oxygen.

5.4 Application Site Reactions

During or immediately after treatment with BONDLIDO, the skin at the site of application may develop blisters, bruising, burning sensation, depigmentation, dermatitis, discoloration, edema, erythema, exfoliation, irritation, papules, petechia, pruritus, vesicles, or may be the locus of abnormal sensation. These reactions are generally mild and transient, resolving spontaneously within a few minutes to hours. If application site reactions occur while the topical system is being worn, advise the patient to remove BONDLIDO and not to reapply until skin reactions subside.

5.5 Hypersensitivity Reactions

Patients allergic to para-aminobenzoic acid (PABA) derivatives (procaine, tetracaine, benzocaine, etc.) have not shown cross-sensitivity to lidocaine. However, be aware of the potential for cross-sensitivity in patients allergic to PABA derivatives, especially if the etiologic agent is uncertain. Manage hypersensitivity reactions by conventional means. The detection of sensitivity by skin testing is of doubtful value.

5.6 Eye Exposure

The contact of BONDLIDO with eyes, although not studied, should be avoided based on findings of severe eye irritation with the application of similar products in animals. If eye contact occurs, immediately wash out the eye with water or saline and protect the eye using, for example, eye glasses/eye wear, until sensation returns.

6 ADVERSE REACTIONS

The following serious adverse reactions are described elsewhere in the labeling:

- Accidental Exposure [see Warnings and Precautions (5.1)]
- Excessive Dosing/Overexposure to Lidocaine [see Warnings and Precautions (5.2)] Methemoglobinemia [see Warnings and Precautions (5.3)]
- Application Site Reactions [see Warnings and Precautions (5.4)]
- Hypersensitivity Reactions [see Warnings and Precautions (5.5)]
- Eye Irritation [see Warnings and Precautions (5.6)]

The following adverse reactions associated with the use of lidocaine were identified in clinical trials or postmarketing reports for lidocaine. Because some of these reactions were reported voluntarily from a population of uncertain size, it is not always possible to reliably estimate their frequency or establish a causal relationship to drug exposure.

Skin and subcutaneous tissues: blisters, bruising, burning sensation, depigmentation, dermatitis, discoloration, edema, erosions, erythema, exfoliation, flushing, irritation, papules, petechia, pruritus, vesicles, and abnormal sensation.

Immune system: angioedema, bronchospasm, dermatitis, dyspnea, hypersensitivity, laryngospasm, pruritus, shock, and urticaria.

Central Nervous System: lightheadedness, nervousness, apprehension, euphoria, confusion, dizziness, drowsiness, tinnitus, blurred or double vision, sensations of heat, cold or numbness, twitching, tremors, convulsions, unconsciousness, somnolence, respiratory depression and arrest.

Cardiovascular: bradycardia, hypotension, and cardiovascular collapse leading to arrest.

Other: asthenia, disorientation, headache, hyperesthesia, hypoesthesia, metallic taste, nausea, pain exacerbated, paresthesia, taste alteration, and vomiting.

7 DRUG INTERACTIONS

7.1 Antiarrhythmic Drugs

When BONDLIDO is used in patients receiving Class I antiarrhythmic drugs (such as tocainide or mexiletine), the toxic effects are additive and potentially synergistic. Consider risk/benefit during concomitant use.

7.2 Local Anesthetics

When BONDLIDO is used concomitantly with other products containing local anesthetic agents, the effects are additive. The amount absorbed from all formulations must be considered for safe use.

7.3 Drugs That May Cause Methemoglobinemia When Used with BONDLIDO

Patients who are administered local anesthetics are at increased risk of developing methemoglobinemia when concurrently exposed to the following drugs, which could include other local anesthetics:

Examples of Drugs Associated with Methemoglobinemia:

Class | Examples
Nitrates/Nitrites | nitric oxide, nitroglycerin, nitroprusside, nitrous oxide
Local anesthetics | articaine, benzocaine, bupivacaine, lidocaine, mepivacaine, prilocaine, procaine, ropivacaine, tetracaine
Antineoplastic agents | cyclophosphamide, flutamide, hydroxyurea, ifosfamide, rasburicase
Antibiotics | dapsone, nitrofurantoin, para-aminosalicylic acid, sulfonamides
Antimalarials | chloroquine, primaquine
Anticonvulsants | Phenobarbital, phenytoin, sodium valproate
Other drugs | acetaminophen, metoclopramide, quinine, sulfasalazine

8 USE IN SPECIFIC POPULATIONS

8.1 Pregnancy

Risk Summary

The limited human data with lidocaine in pregnant woman are not sufficient to inform drug-associated risk for major birth defects and miscarriage.

The use of lidocaine for labor neuraxial analgesia has not been associated with an increased incidence of adverse fetal effects either during delivery or during the neonatal period [see Data]. Should BONDLIDO be used concomitantly with other products containing lidocaine, consider total drug doses contributed by all formulations.

In a published animal reproduction study, pregnant rats administered lidocaine by continuous subcutaneous infusion at a dose approximately 12 times the maximum recommended daily dose (MRDD) of 400 mg in BONDLIDO during the period of organogenesis resulted in lower fetal body weights. In a published animal reproduction study, pregnant rats administered lidocaine, containing 1:100,000 epinephrine, injected into the masseter muscle of the jaw or into the gum of the lower jaw at approximately 0.14 times the MRDD on Gestation Day 11 resulted in developmental delays in neonates [see Data].

The background risk of major birth defects and miscarriage for the indicated population is unknown. All pregnancies carry some risk of birth defects, loss, or other adverse outcomes. In the U.S. general population, the estimated background risk of major birth defects and miscarriage in clinically recognized pregnancies is 2% to 4% and 15% to 20%, respectively.

Data

Human Data

In 22 parturient women given 1.5% lidocaine epidural anesthesia, there were no effects on neonatal behavior, using the early neonatal neurobehavioral scale (ENNS). Neuraxial analgesia also did not affect fetal heart rate, beat-to-beat variability, or uterine activity.

Animal Data

Reproductive studies with lidocaine have been performed in rats at doses up to 30 mg/kg (0.73 times the maximum recommended daily dose [MRDD] of 400 mg from BONDLIDO on a mg/m ^2 basis) subcutaneously and have revealed no evidence of harm to the fetus due to lidocaine.

In a published study, lidocaine administered to pregnant rats by continuous subcutaneous infusion during the period of organogenesis at 100, 250, and 500 mg/kg/day, did not produce any structural abnormalities, but did result in lower fetal weights at 500 mg/kg/day dose (approximately 12 times the MRDD on a mg/m ^2 basis) in the absence of maternal toxicity.

In a published study, lidocaine containing 1:100,000 epinephrine at a dose of 6 mg/kg (approximately 0.14 times the MRDD on a mg/m^2 basis) injected into the masseter muscle of the jaw or into the gum of the lower jaw of pregnant Long-Evans hooded rats on Gestation Day 11 resulted in developmental delays in the neonates. Developmental delays were observed for negative geotaxis, static righting reflex, visual discrimination response, sensitivity and response to thermal and electrical shock stimuli, and water maze acquisition. The developmental delays of the neonatal animals were transient, with responses becoming comparable to untreated animals later in life. The clinical relevance of these animal data is uncertain.

8.2 Lactation

Risk Summary

Lidocaine is excreted into human milk. A milk:plasma ratio of 1.07 (for AUC) was observed when lidocaine was used as an epidural anesthetic for cesarean section in 27 women. Lactating women undergoing a dental procedure had a 0.4 milk:plasma ratio. In another dental procedure study, a single patient was administered 20 mg of lidocaine and the milk:plasma ratio was reported as 1.1 at five to six hours after injection. These data, and the low concentrations of lidocaine in the plasma after topical administration of BONDLIDO in recommended doses, suggest that a small amount of lidocaine would be ingested orally by a suckling infant. However, caution should be exercised when BONDLIDO is administered to a nursing mother, especially when administered with other local anesthetics.

8.4 Pediatric Use

Safety and effectiveness in pediatric patients have not been established.

8.5 Geriatric Use

Clinical studies of BONDLIDO did not include sufficient numbers of subjects aged 65 and over to determine whether they respond differently from younger subjects. Other reported clinical experience has not identified differences in responses between the elderly and younger patients. In general, dose selection for an elderly patient should be done with caution, usually starting at the low end of the dosing range, reflecting the greater frequency of decreased hepatic, renal, or cardiac function, and of concomitant disease or other drug therapy.

10 OVERDOSAGE

Lidocaine overdose from cutaneous absorption is rare but could occur. If there is any suspicion of lidocaine overdose, drug blood concentration should be checked. The management of overdose includes close monitoring, supportive care, and symptomatic treatment. Dialysis is of negligible value in the treatment of acute overdose with lidocaine.

In the absence of massive topical overdose or oral ingestion, evaluation of symptoms of toxicity should include consideration of other etiologies for the clinical effects, or overdosage from other sources of lidocaine or other local anesthetics.

11 DESCRIPTION

BONDLIDO (lidocaine topical system) 10% is a drug-in-adhesive topical delivery system containing 200 mg lidocaine with a non-woven polyethylene terephthalate (PET) backing membrane and a PET film release liner.

Lidocaine, an amide local anesthetic, is chemically designated as acetamide, 2-(diethylamino)-N-(2,6-dimethylphenyl) (C14H22N2O), has a molecular weight of 234.34 g/mol, an octanol:water partition ratio of 43 at pH 7.4, is very soluble in methanol and in ethanol, is soluble in acetic acid and in diethyl ether, is practically in-soluble in water, dissolves in dilute hydrochloric acid, and has the following structure:

Each BONDLIDO topical system is 10 cm × 14 cm × 0.066 cm and contains the following inactive ingredients: blue ink, hydrocarbon, lactic acid, mono- and di-glycerides, non-woven PET backing membrane, PET film, polyoxyl 40 hydrogenated castor oil, propylene carbonate, styrene/isoprene/styrene block copolymer, tartaric acid, and terpene resin.

12 CLINICAL PHARMACOLOGY

12.1 Mechanism of Action

Lidocaine is an amide-type local anesthetic and is suggested to stabilize neuronal membranes by inhibiting the ionic fluxes required for the initiation and conduction of impulses.

12.2 Pharmacodynamics

The penetration of lidocaine into intact skin after application of BONDLIDO is sufficient to produce an analgesic effect, but less than the amount necessary to produce a complete sensory block.

12.3 Pharmacokinetics

Bioavailability for topical systems such as BONDLIDO is dependent on multiple factors, including formulation, and does not necessarily correlate with dosage strength. In a single-dose, crossover study conducted in 32 healthy volunteers, BONDLIDO (lidocaine topical system 10%) demonstrated equivalent systemic exposure (AUC) and peak concentration (C max) of lidocaine to a lidocaine topical system 5%.

Absorption

The amount of lidocaine systemically absorbed from BONDLIDO topical system is directly related to both the duration of application and the surface area over which it is applied.

In a pharmacokinetic study, two BONDLIDO topical systems were applied on the back of the healthy volunteers for 12 hours. Blood samples were drawn for determination of lidocaine concentration during the topical system application and for 32 hours after removal of topical systems. The results are summarized in Table 1.

Table 1. Mean ± SD Pharmacokinetic Parameters of lidocaine from BONDLIDO in healthy volunteers (n = 32, 12-hour application time)
 | Application Site | Area (cm^2) | Cmax (ng/mL) | AUC0-inf (ng∙hr/mL) | Tmax (hr) [median (min, max)]
2 BONDLIDO topical system (2 × 200 mg = 400 mg total dose for 12 hours) | Back | 280 | 52.8 (38.9) | 837 (37.7) | 13.0 (8.0,18.0)

Repeated application of three lidocaine topical systems 5% simultaneously for 12 hours (recommended maximum daily dose), once per day for three days, indicated that the lidocaine concentration does not increase with daily use. The mean plasma pharmacokinetic profile for the 15 healthy volunteers is shown in Figure 1.

Figure 1. Mean lidocaine blood concentrations after three consecutive daily applications of three lidocaine topical systems 5% simultaneously for 12 hours per day in healthy volunteers (n = 15)

The pharmacokinetics of lidocaine delivered by BONDLIDO topical system was assessed in 20 healthy volunteers undergoing exercise (four 30 minute sessions of moderate exercise over the 12 hour period of BONDLIDO application) and following application of a transparent film occlusive dressing over BONDLIDO for the full 12 hour period of BONDLIDO application (occlusion) and results were compared to those obtained under resting conditions. Two hours of moderate exercise resulted in approximately 20% reduction in systemic exposure as measured by Cmax and AUC[0-inf] indicating a modest reduction in delivery from the topical system over the 12 hour period of topical system application. Exposure to total occlusion of the topical system for 12 hours produced no statistically significant changes in the absorption or pharmacokinetics of lidocaine from BONDLIDO topical system.

Distribution

When lidocaine is administered intravenously to healthy volunteers, the volume of distribution is 0.7 to 2.7 L/kg (mean 1.5 ± 0.6 SD, n = 15). At concentrations produced by application of a lidocaine topical system 5%, lidocaine is approximately 70% bound to plasma proteins, primarily alpha-1-acid glycoprotein. At much higher plasma concentrations (1 to 4 µg/mL of free base), the plasma protein binding of lidocaine is concentration dependent. Lidocaine crosses the placental and blood brain barriers, presumably by passive diffusion.

Elimination

Metabolism:

It is not known if lidocaine is metabolized in the skin. Lidocaine is metabolized rapidly by the liver to a number of metabolites, including monoethylglycinexylidide (MEGX) and glycinexylidide (GX), both of which have pharmacologic activity similar to, but less potent than that of lidocaine. A minor metabolite, 2,6-xylidine, has unknown pharmacologic activity. The blood concentration of this metabolite is negligible following application of lidocaine topical system 5%. Following intravenous administration, MEGX and GX concentrations in serum range from 11 to 36% and from 5 to 11% of lidocaine concentrations, respectively.

Excretion:

Lidocaine and its metabolites are excreted by the kidneys. Less than 10% of lidocaine is excreted unchanged. The half-life of lidocaine elimination from the plasma following IV administration is 81 to 149 minutes (mean 107 ± 22 SD, n = 15). The systemic clearance is 0.33 to 0.90 L/minute (mean 0.64 ±0.18 SD, n = 15).

13 NONCLINICAL TOXICOLOGY

13.1 Carcinogenesis, Mutagenesis, Impairment of Fertility

Carcinogenesis

Long-term studies in animals to evaluate the carcinogenic potential of BONDLIDO have not been conducted.

A metabolite, 2,6-xylidine, has been found to be carcinogenic in rats. The clinical significance is not known.

Mutagenesis

Lidocaine HCl was not mutagenic in the Salmonella/mammalian microsome test (Ames assay) and was not clastogenic in the chromosome aberration assay with human lymphocytes or in the mouse micronucleus test.

Impairment of Fertility

In a published study, female Sprague-Dawley rats were treated subcutaneously with lidocaine via osmotic pumps starting two weeks prior to mating, and reproductive effects were assessed. Rats dosed up to the high dose of 500 mg/kg/day (approximately 12 times the MRDD on a mg/m^2 basis) showed no effects on copulatory rate, pregnancy rate, or the numbers of corpora lutea or implantations.

14 CLINICAL STUDIES

Single-dose treatment with a different lidocaine topical system was compared to treatment with vehicle system (without lidocaine), and to no treatment (observation only) in a double-blind, crossover clinical trial with 35 post-herpetic neuralgia patients. Pain intensity and pain relief scores were evaluated periodically for 12 hours. Lidocaine topical system performed statistically better than vehicle system in terms of pain intensity from 4 to 12 hours.

Multiple-dose, two-week treatment with a different lidocaine topical system was also compared to vehicle system (without lidocaine) in a double-blind, crossover clinical trial of withdrawal-type design conducted in 32 patients, who were considered as responders to the open-label use of lidocaine topical system prior to the study. The constant type of pain was evaluated but not the pain induced by sensory stimuli (dysesthesia).

Statistically significant differences favoring the lidocaine topical system were observed in terms of time to exit from the trial (14 versus 3.8 days at p-value <0.001), daily average pain relief, and patient's preference of treatment. About half of the patients also took oral medication commonly used in the treatment of post-herpetic neuralgia. The extent of use of concomitant medication was similar in the two treatment groups.

Based on a clinical study in adults wearing BONDLIDO covering the thoracic dermatomes T8-T10, 98 of 100 topical systems applied exhibited 75% or greater surface area adhesion at all timepoints evaluated (every 3 hours) throughout the 12-hour wear period.

16 HOW SUPPLIED/STORAGE AND HANDLING

BONDLIDO (lidocaine topical system) 10% is a rectangular topical system with blue printing on one side and release liner on other. It is available as the following:

Carton of 28 topical systems, packaged into individual child-resistant pouches.

NDC 83708-111-28

STORAGE AND HANDLING

Store at 20°C to 25°C (68°F to 77°F); excursions permitted between 15°C to 30°C (59°F to 86°F) [see USP Controlled Room Temperature]. Protect from light.

17 PATIENT COUNSELING INFORMATION

Advise the patient to read the FDA-approved patient labeling (Instructions for Use).

Accidental Exposure and Disposal

Advise patients to store BONDLIDO out of the reach of children, pets, and others. Advise patients to dispose of used BONDLIDO by folding used BONDLIDO so that the adhesive side sticks to itself and safely discarding used BONDLIDO where children, pets, and others cannot come in contact with them. [see Dosage and Administration (2), Warnings and Precautions (5.2)]

Proper Application

Advise patients:

- to avoid getting BONDLIDO wet (e.g., bathing, swimming or showering) [see Dosage and Administration (2)].
- not to apply more than the prescribed number (up to 2 BONDLIDO) [see Dosage and Administration (2), Warnings and Precautions (5.2)].
- not to wear BONDLIDO longer than the recommended wearing time (12 hours of every 24 hours) [see Dosage and Administration (2), Warnings and Precautions (5.2)].
- not to apply BONDLIDO to non-intact skin [see Warnings and Precautions (5.2)].

Methemoglobinemia

Inform patients that use of local anesthetics may cause methemoglobinemia, a serious condition that must be treated promptly. Advise patients or caregivers to stop use and seek immediate medical attention if they or someone in their care experience the following signs or symptoms: pale, gray, or blue colored skin (cyanosis); headache; rapid heart rate; shortness of breath; lightheadedness; or fatigue [see Warnings and Precautions (5.3)].

Application Site Reactions

Inform patients that skin irritation and other skin reactions may occur at the site of BONDLIDO application. If skin reactions occur during wear, instruct patients to remove BONDLIDO and not to reapply until the skin reaction subsides [see Warnings and Precautions (5.4)].

Eye Exposure

Advise patients to wash hands immediately after handling BONDLIDO and to avoid contact with eyes. Instruct patients to, if eye contact should occur, immediately wash out the eye with water or saline and protect the eye until sensation returns [see Dosage and Administration (2), Warnings and Precautions (5.5)].

Manufactured for:
MEDRx USA, Inc.
2030 Main St., Suite 1300
Irvine, CA 92614
USA

BONDLIDO Patented. See www.bondlido.com.

MEDRx USA, Inc.

PATIENT INFORMATION
BONDLIDO (BAHND-LYE-DOH)
(lidocaine topical system)

What is BONDLIDO?
BONDLIDO is a prescription medicine used in adults for the relief of pain from damaged nerves (neuropathic pain) that follows healing of shingles.
It is not known if BONDLIDO is safe and effective in children.

Do not use BONDLIDO if you:

- have a history of allergic reactions to numbing medicines (local anesthetics). Ask your healthcare provider if you are not sure.
- are allergic to any of the ingredients in BONDLIDO. See the end of this leaflet for a complete list of ingredients in BONDLIDO.

Before using BONDLIDO, tell your healthcare provider about all of your medical conditions, including if you:

- have liver problems
- have heart or lung problems
- are allergic to numbing medicines such as procaine, tetracaine, or benzocaine
- have been told that you have glucose-6-phosphate dehydrogenase deficiency
- were born with (congenital) methemoglobinemia or have had methemoglobinemia from an unknown cause
- are pregnant or plan to become pregnant. It is not known if BONDLIDO will harm your unborn baby.
- are breastfeeding or plan to breastfeed. BONDLIDO can pass into your breast milk. Talk to your healthcare provider about the best way to feed your baby if you use BONDLIDO.

Tell your healthcare provider about all the medicines you take, including prescription and over-the-counter medicines, vitamins, and herbal supplements. Especially, tell your healthcare provider if you are using other lidocaine containing products or anesthetic medicines.

How should I use BONDLIDO?
Read the Instructions for Use at the end of this Patient Information leaflet for information about how to apply BONDLIDO.

- Use BONDLIDO exactly as your healthcare provider tells you to use it.
- Do not apply more than your prescribed number of BONDLIDO. You may apply up to 2 BONDLIDO topical systems at one time.
- A BONDLIDO topical system may be worn only 1 time for up to 12 hours within a 24-hour period (12 hours on and 12 hours off).
- Apply BONDLIDO to intact skin only. Do not apply BONDLIDO to skin that is not intact, such as skin that is cut, scraped, burned or irritated.
- If the BONDLIDO you are wearing comes off completely and will not stick to your skin, throw it away as described below. You may apply a replacement (a new) BONDLIDO topical system. Take off the replacement BONDLIDO at your usual removal time. The total time you may wear the used and replacement BONDLIDO is 12 hours.
- To remove and properly throw away (dispose of) BONDLIDO, fold the used BONDLIDO so that the sticky sides stick together. Safely throw away the used BONDLIDO where children, pets, and others cannot get to them.
- You may wear clothing over the BONDLIDO application site.
- Do not apply external heat sources, such as heating pads or electric blankets, directly on BONDLIDO. This may cause increased levels of lidocaine in your blood.
- Avoid contact with water, such as bathing, swimming, or showering, while using BONDLIDO. BONDLIDO may not stick if it gets wet.
- Wash your hands right away after handling BONDLIDO (after you apply BONDLIDO, when you try to re-attach it, or when you remove it).
- If you start feeling irritation or burning when applying BONDLIDO, remove BONDLIDO. Do not reapply BONDLIDO until the irritation or burning goes away.
- If you apply more than 2 BONDLIDO topical systems or apply BONDLIDO for longer than 12 hours of a 24-hour period, call your healthcare provider.

What should I avoid while using BONDLIDO?
Avoid contact of your hands and fingers with your eyes while handling BONDLIDO. Contact of BONDLIDO with your eyes can cause severe eye irritation. Wash your hands right away after handling BONDLIDO. If the medicine in BONDLIDO comes in contact with your eye, wash out your eye with water or saline right away. Protect the eye (for example with eye glasses or eye wear) until the numbness goes away.

What are the possible side effects of BONDLIDO?
BONDLIDO may cause serious side effects, including:

- Lidocaine overdose can happen if you apply more than the prescribed number of BONDLIDO, apply BONDLIDO for longer than 12 hours, have liver problems, use BONDLIDO on skin that is not intact, or if you apply external heat sources directly on BONDLIDO. This can result in increased levels of lidocaine in your blood. See "How should I use BONDLIDO?" for information on how to use BONDLIDO.
- A serious blood problem called methemoglobinemia. Methemoglobinemia is a serious blood problem where too much methemoglobin is produced in the blood. Methemoglobinemia can happen with the use of local anesthetics and may not let enough oxygen reach the organs and tissues in your body. Anyone who uses or receives local anesthetics is at risk for methemoglobinemia, but certain people are more likely to have serious medical problems and need to be closely monitored by their healthcare provider during treatment with BONDLIDO, including:
  - people with glucose-6-phosphate dehydrogenase deficiency
  - people with heart or lung problems
  - babies under 6 months of age (BONDLIDO is not approved for use in children)
  - people who were born with (congenital) or who have had methemoglobinemia from an unknown cause
  - people exposed to certain chemicals at the same time that they use or receive local anesthetic
  Signs of methemoglobinemia can happen right away or they may not happen for some hours after you have used or received a local anesthetic. It is important to get medical treatment right away to help prevent more serious side effects including seizures, coma, abnormal heart rhythms, and death. Stop using BONDLIDO and get medical help right away if you develop any of the following signs or symptoms:

- pale, gray, or blue colored skin
- headache

- rapid heart beat
- shortness of breath

- lightheadedness
- tiredness

- Application site reactions. Skin irritation and other skin reactions at the BONDLIDO application site are common and are usually mild. These reactions can happen during or right after treatment with BONDLIDO. Application site reactions will usually go away within a few minutes to hours. Severe skin irritation may happen with BONDLIDO if you use it for a longer time than instructed. If you develop a skin reaction while wearing BONDLIDO, remove it. Do not reapply BONDLIDO until the site reaction goes away. Symptoms of application site reactions may include:

- blisters
- bruising
- burning or abnormal sensation
- change or loss of color of your skin
- swelling, redness, and pain of the skin

- peeling or flaking of skin
- irritation
- pimple-like raised skin
- itching

- Allergic reactions can happen if you have a history of allergic reactions to numbing medicines (anesthetics). Tell your healthcare provider right away if you have any symptoms of an allergic reaction such as swelling or shortness of breath.

These are not all the possible side effects of BONDLIDO.
Call your doctor for medical advice about side effects. You may report side effects to FDA at 1-800-FDA-1088.

How should I store BONDLIDO?

- Store BONDLIDO at room temperature between 68°F to 77°F (20°C to 25°C).
- Do not store BONDLIDO outside the sealed pouch.
- Protect BONDLIDO from light.
- Each BONDLIDO topical system comes in a child-resistant pouch.

Keep BONDLIDO and all medicines out of the reach of children, pets, and others.

General information about the safe and effective use of BONDLIDO.
Medicines are sometimes prescribed for purposes other than those listed in a Patient Information leaflet. Do not use BONDLIDO for a condition for which it was not prescribed. Do not give BONDLIDO to other people, even if they have the same symptoms that you have. It may harm them. You can ask your pharmacist or healthcare provider for information about BONDLIDO that is written for health professionals.

What are the ingredients in BONDLIDO?
Active ingredient: lidocaine
Inactive ingredients: blue ink, hydrocarbon, lactic acid, mono- and di-glycerides, non-woven PET backing membrane, PET film, polyoxyl 40 hydrogenated castor oil, propylene carbonate, styrene/isoprene/styrene block copolymer, tartaric acid, and terpene resin.
Manufactured for: MEDRx USA, Inc., 2030 Main St., Suite 1300, Irvine, CA 92614, USA
For more information, go to www.bondlido.com or call 1-844-633-5436.

This Patient Information has been approved by the U.S. Food and Drug Administration.

Issued: 09/2025

INSTRUCTIONS FOR USE

BONDLIDO [BAHND-LYE-DOH]
(lidocaine topical system)

This Instruction for Use contains information on how to apply, remove, and dispose of BONDLIDO. Read this Instructions for Use before you start using BONDLIDO and each time you get a refill. There may be new information. This information does not take the place of talking to your healthcare provider about your medical treatment or conditions.

Important Information You Need to Know Before Using BONDLIDO:

- BONDLIDO is for topical use only (apply on top of skin).
- Apply the prescribed number of BONDLIDO at one time.
- Do not apply more than your prescribed number of BONDLIDO. You may apply up to 2 BONDLIDO topical systems at one time.
- BONDLIDO may be worn only 1 time for up to 12 hours within a 24-hour period (12 hours on and 12 hours off).
- Apply BONDLIDO to intact skin only. Do not apply BONDLIDO to skin that is not intact, such as skin that is cut, scraped, burned or irritated.
- If the BONDLIDO you are wearing comes off completely and will not stick to your skin, see "How to apply a replacement (a new) BONDLIDO:"
- You may wear clothing over the BONDLIDO application site.
- Do not apply external heat sources, such as heating pads or electric blankets, directly on BONDLIDO. This may cause increased levels of lidocaine in your blood.
- Avoid contact with water, such as bathing, swimming, or showering while using BONDLIDO. BONDLIDO may not stick if it gets wet.
- Store BONDLIDO out of the reach of children, pets, and others.

Applying BONDLIDO:

Step 1: Select the application site.

- BONDLIDO should only be applied to clean, dry, and intact skin to cover the most painful area.

Step 2: Using scissors, carefully cut the pouch along the dotted line and open it to remove BONDLIDO.

- Do not use BONDLIDO if it is damaged. Throw it away and get a new one.
- Do not open the BONDLIDO pouch until you are ready to use it.
- Apply BONDLIDO right away after removing it from the pouch.

Step 3a: Remove the center part of the transparent release liner (clear plastic backing).

Apply the adhesive (sticky) side of the center part of BONDLIDO onto your skin.

- Apply BONDLIDO to intact skin only.
- Do not touch the sticky side with your fingers.

Step 3b: While removing the right part of the clear plastic backing with one hand, use your other hand to apply BONDLIDO onto your skin and smooth it down with your fingers.

- Do not touch the sticky side with your fingers.

Step 3c: Hold the left part of the clear plastic backing, then slowly peel it away and smooth BONDLIDO down onto your skin with your fingers.
Press BONDLIDO firmly with the palm of your hand for 20 seconds to make sure it sticks well to your skin.

Step 4: Wash your hands right away after applying BONDLIDO.

- Avoid contact of your hands or fingers with your eyes until your hands are washed.

Removing and disposing of BONDLIDO:

Step 5: Remove BONDLIDO from your skin after you have worn it for up to 12 hours.

- Fold the used BONDLIDO so that the sticky sides stick together.

Step 6: Throw away (dispose of) the used BONDLIDO where children, pets, and others cannot get to them.

- Wash your hands right away after removing BONDLIDO.

How to apply a replacement (a new) BONDLIDO:

- If the BONDLIDO you are wearing comes off completely and will not stick to your skin, throw away the used BONDLIDO as instructed above in Steps 5 and 6.
- You may apply a replacement BONDLIDO the same way you would apply a new BONDLIDO as described above in Steps 1 through 4.
- Take off the replacement BONDLIDO at your usual removal time.
- The total time you may wear the used and replacement BONDLIDO is 12 hours. You should not wear BONDLIDO for more than 12 hours within a 24-hour period.

Storing BONDLIDO:

- Store BONDLIDO at room temperature between 68°F to 77°F (20°C to 25°C).
- Do not store BONDLIDO outside the sealed pouch.
- Protect BONDLIDO from light.
- Each BONDLIDO topical system comes in a child-resistant pouch.

Store BONDLIDO and all medicines out of the reach of children, pets, and others.

Manufactured for: MEDRx USA, Inc., 2030 Main St., Suite 1300, Irvine, CA 92614, USA

For more information, go to www.bondlido.com or call 1-844-633-5436.

This Instructions for Use has been approved by the U.S. Food and Drug Administration.
Approved: 09/2025

PRINCIPAL DISPLAY PANEL - 28 Patch Pouch Carton

NDC: 83708-1111-28
Rx Only

BONDLIDO®
lidocaine topical system 10%

For topical use only
28 topical systems
1 Pouch containing 1 Topical System Each

MEDRx®